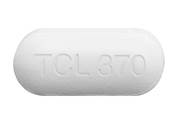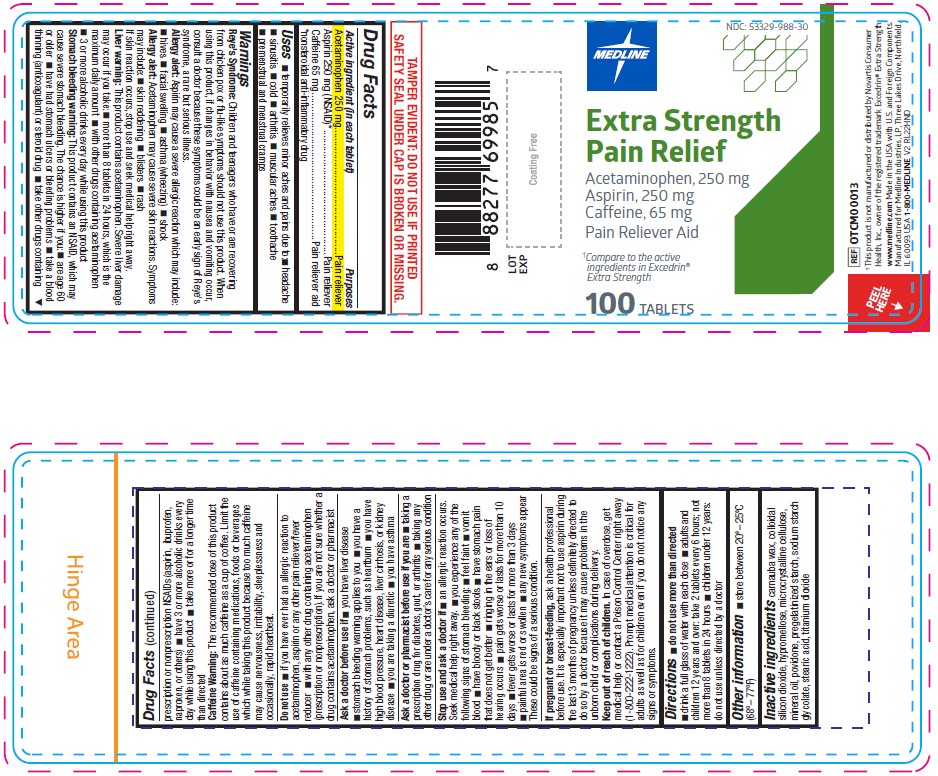 DRUG LABEL: Extra Pain Relief Acetaminophen, Aspirin (NSAID) and Caffeine
NDC: 53329-988 | Form: TABLET, FILM COATED
Manufacturer: Medline Industries, LP
Category: otc | Type: HUMAN OTC DRUG LABEL
Date: 20250224

ACTIVE INGREDIENTS: ASPIRIN 250 mg/1 1; CAFFEINE 65 mg/1 1; ACETAMINOPHEN 250 mg/1 1
INACTIVE INGREDIENTS: SILICON DIOXIDE; TITANIUM DIOXIDE; STARCH, PREGELATINIZED CORN; SODIUM STARCH GLYCOLATE TYPE A CORN; CARNAUBA WAX; HYPROMELLOSE, UNSPECIFIED; MICROCRYSTALLINE CELLULOSE; MINERAL OIL; POVIDONE; STEARIC ACID

988 Extra Pain Relief Acetaminophen, Aspirin (NSAID) and Caffeine

Active ingredient (in each tablet)

Acetaminophen 250 mg

Aspirin 250 mg (NSAID)*

Caffeine 65 mg

*nonsteroidal anti-inflammatory drug

Purpose

Pain reliever

Pain reliever

Pain reliever aid

Uses

- temporarily relieves minor aches and pains due to:
- headache
- sinusitis
- cold
- arthritis
- muscular aches
- toothache
- premenstual and menstrual cramps

Warnings

Reye's Syndrome: Children and teenagers who have or are recovering from chicken pox or flu-like symptoms should not use this product. When using this product, if changes in behavior with nausea and vomiting occur, consult a doctor because these symptoms could be an early sign of Reye's syndrome, a rare but serious illness.
Allergy alert: Aspirin may cause a severe allergic reaction which may include:

- hives
- facial swelling
- asthma (wheezing)
- shock

Allergy alert: Acetaminophen may cause severe skin reactions. Symptoms may include:

- skin reddening
- blisters
- rash

If skin reaction occurs, stop use and seek medical help right away.
Liver Warning: This product contains acetaminophen. Severe liver damage may occur if you take:

- more than 8 tablets in 24 hours, which is the maximum daily amount
- with other drugs containing acetaminophen
- 3 or more alcoholic drinks every day while using this product

Stomach bleeding warning: This product contains an NSAID, which may cause severe stomach bleeding. The chance is higher if you:

- are age 60 or older
- have had stomach ulcers or bleeding problems
- take a blood thinning (anticoagulant) or steroid drug
- take other drugs containing prescription or nonprescription NSAIDs (aspirin, ibuprofen, naproxen, or others)
- have 3 or more alcoholic drinks every day while using this product
- take more or for a longer time than directed

Caffeine Warning: The recommended dose of this product contains about as much caffeine as a cup of coffee. Limit the use of caffeine containing medications, foods or beverages which while taking this product because too much caffeine may cause nervousness, irritability, sleeplessness and occasionally, rapid heartbeat.

Do not use

- if you have ever had an allergic reaction to acetaminophen, aspirin or any other pain reliever/fever reducer
- with any other drug containing acetaminophen (prescription or nonprescription). If you are not sure whether a drug contains acetaminophen, ask a doctor or pharmacist.
- for more than 10 days for pain unless directed by a doctor
- for more than 3 days for fever unless directed by a doctor

Ask doctor before use if

- stomach bleeding warning applies to you
- you have a history of stomach problems, such as heartburn
- you have high blood pressure, heart disease, liver cirrhosis, or kidney disease
- you are taking a diuretic
- you have asthma
- you have liver disease

Stop using and ask a doctor if

- an allergic reaction occurs. Seek medical help right away.
- painful area is red or swollen
- symptoms do not improve
- any new symptoms appear
- pain or fever persists or gets worse
- you experience any of the following signs of stomach bleeding:
- feel faint
- vomit blood
- have bloody or black stools
- have stomach pain that does not get better
- if ringing in the ears or a loss of hearing occurs, consult a doctor before taking any more of this product
- fever gets worse or lasts for more than 3 days
- pain gets worse or lasts for more than 10 days

If pregnant or breast-feeding,

ask a health professional before use. It is especially important not to use aspirin during the last 3 months of pregnancy unless definitely directed to do so by a doctor because it may cause problems in the unborn child or complications during delivery.

Keep out of reach of children.

In case of accidental overdose, get medical help or contact a Poison Control Center right away. Prompt medical attention is critical for adults as well as for children even if you do not notice any signs or symptoms.

Directions

- do not use more than directed
- drink a full glass of water with each dose
- adults and children 12 years and over: take 2 tablets every 6 hours; not more than 8 tablets in 24 hours
- children under 12 years: do not use unless directed by a doctor

Other information

- store at 20°-25°C (68°-77°F)

Inactive ingredients

carnauba wax, colloidal silicon dioxide, hypromellose, microcrystalline cellulose, mineral oil, povidone, pregelatinized starch, sodium starch glycolate, stearic acid, titanium dioxide

Manufacturing Information

Manufactured for:
Medline Industries, LP
Three Lakes Drive, Northfield, IL 60093 USA
Made in USA with domestic and foreign materials
www.medline.com
1-800-MEDLINE (633-5463)
REF: OTCM00013
V1 RE22HND

†This product is not manufactured or distributed by Novartis Consumer Health, Inc., owner of the registered trademark Excedrin® Extra Strength.